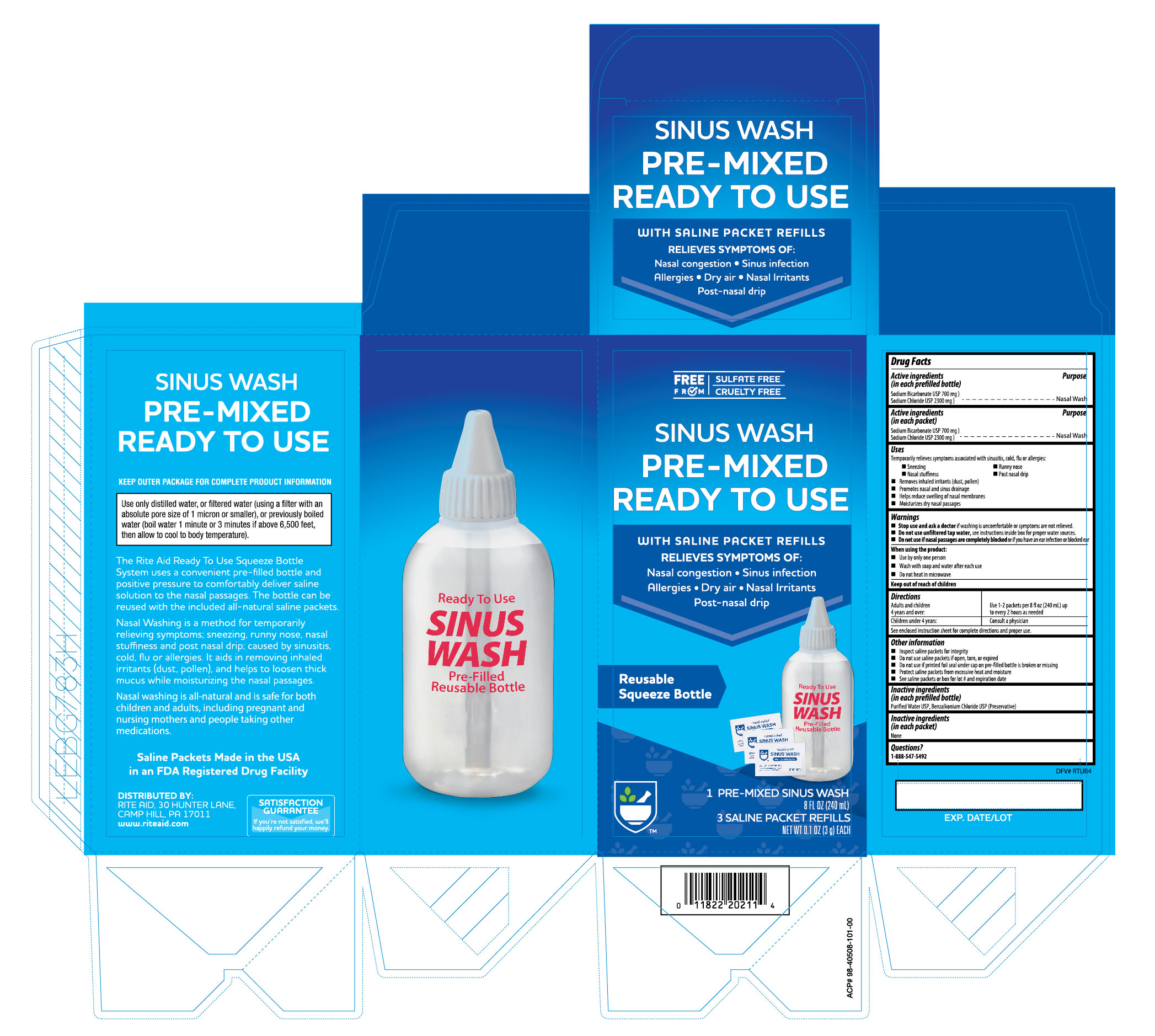 DRUG LABEL: Sinus Wash Pre Mixed Ready to Use
NDC: 11822-0472 | Form: KIT | Route: NASAL
Manufacturer: RITE AID CORPORATION
Category: otc | Type: HUMAN OTC DRUG LABEL
Date: 20251210

ACTIVE INGREDIENTS: SODIUM CHLORIDE 77.8 mg/100 mg; SODIUM BICARBONATE 22.8 mg/100 mg; SODIUM BICARBONATE 22.2 mg/0.1 g; SODIUM CHLORIDE 77.8 mg/0.1 g
INACTIVE INGREDIENTS: WATER; WATER; BENZALKONIUM CHLORIDE

Rite Aid Sinus Wash Pre-Mixed Ready to Use

Active Ingredients

(in each prefilled bottle)

Sodium Bicarbonate USP 700 mg

Sodium Chloride USP 2300 mg

Active ingredients

(in each packet)

Sodium Bicarbonate USP 700 mg

Sodium Chloride USP 2300 mg

Purpose

Nasal Wash

Purpose

Nasal Wash

Uses

Temporarily relieves symptoms associated with

sinusitis, cold, flu or allergies:

-Sneezing

-Runny nose

-Nasal stuffiness

-Post nasal drip

-Removes inhaled irritants (dust, pollen)

-Promotes nasal and sinus drainage

-Helps reduce swelling of nasal membranes

-Moisturizes dry nasal passages

Warnings

Stop use and ask a doctor if washing is uncomfortable or

symptoms are not reduced.

Do not use unfiltered tap water. See instructions inside box

for proper water sources.

Do not use if nasal passages are completely blocked or if you

have an ear infection or blocked ears.

When using this product:

- Use by only one person
- Wash with soap and water after each use
- Do not heat in microwave

Keep out of reach of children

Directions:

Adults and children 4 years and over: use 1 - 2 packets per 8 fl. oz (240 mL) up to every 2 hours as needed

Children under 4 years: Consult a physician

Prior to first use see enclosed instruction sheet for complete directions

Other information

- Inspect saline packets for integrity
- Do not use saline packets if open or torn
- Protect saline packets from excessive heat and moisture
- See saline packets or box for lot no. and expiration date

Inactive ingredients

(in each prefilled bottle)

Purified Water USP, Benzalkonium Chloride USP (Preservative)

Inactive ingredients

(in each packet)

None

Questions?

1-888-547-5492